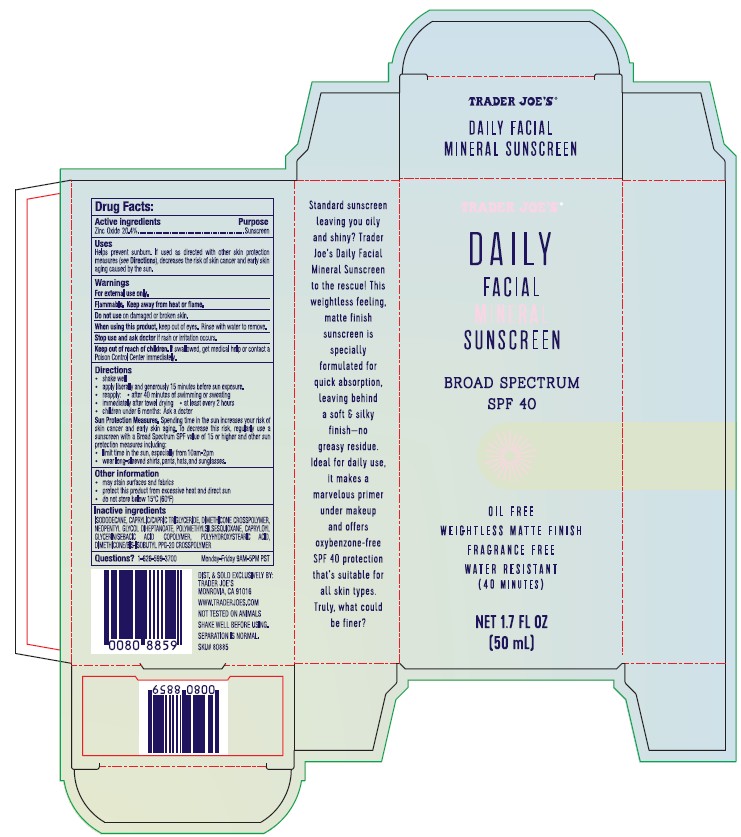 DRUG LABEL: TRADER JOES DAILY FACIAL MINERAL SUNSCREEN
NDC: 71270-161 | Form: LOTION
Manufacturer: Trader Joe's Company
Category: otc | Type: HUMAN OTC DRUG LABEL
Date: 20250326

ACTIVE INGREDIENTS: ZINC OXIDE 20.4 g/100 g
INACTIVE INGREDIENTS: ISODODECANE; DIMETHICONE CROSSPOLYMER; NEOPENTYL GLYCOL DIHEPTANOATE; POLYMETHYLSILSESQUIOXANE (11 MICRONS); MEDIUM-CHAIN TRIGLYCERIDES; CAPRYLOYL GLYCERIN/SEBACIC ACID COPOLYMER (2000 MPA.S); POLYHYDROXYSTEARIC ACID (2300 MW); DIMETHICONE/BIS-ISOBUTYL PPG-20 CROSSPOLYMER

TRADER JOE’S (as PLD) - DAILY FACIAL MINERAL SUNSCREEN SPF 40 (71270-161)

Active ingredient

Zinc Oxide 20.4%

Purpose

Sunscreen

Uses

- Helps prevent sunburn.
- If used as directed with other sun protection measures (see Directions), decreases the risk of skin cancer and early skin aging caused by the sun.

Warnings

For external use only.

Do not use on damaged or broken skin.

When using this product, keep out of eyes. Rinse with water to remove.

Stop use and ask a doctor if rash or irritation occurs.

Keep out of reach of children. If swallowed, get medical help or contact a Poison Control Center immediately.

Directions

- shakewell
- apply liberally and generously 15 minutes before sun exposure.
- Reapply:
- after 40 minutes of swimming or sweating
- immediately after towel dryng
- at least every 2hours
- children under 6 months: ask a doctor

Sun Protection Measures. Spendng time in the sun increases your risk of skin cancer and early skin aging. To decrease this risk, regularly use a sunscreen with a Broad Spectrum SPF value of 15 or higher and other sun protection measures including:

- limit time in the sun,especially from10am-2pm
- wear long-sleeved shirts, pants, hats, and sunglasses.

Other information

- may stain surfaces and fabrics
- protect this product from excessive heat and direct sun
- do not store below 15°C (60°F)

Inactive ingredients

ISODODECANE, CAPRYLIC/CAPRIC TRIGLYCERIDE, DIMETHICONE CROSSPOLYMER, NEOPENTYL GLYCOL DIHEPTANOATE, POLYMETHYLSILSESQUIOXANE, CAPRYLOYL GLYCERIN/SEBACIC ACID COPOLYMER, POLYHYDROXYSTEARIC ACID, DIMETHICONE/BIS-ISOBUTYL PPG-20 CROSSPOLYMER

Questions or comments?

1- 626-599-3700

Monday – Friday 9 AM – 5 PM PST